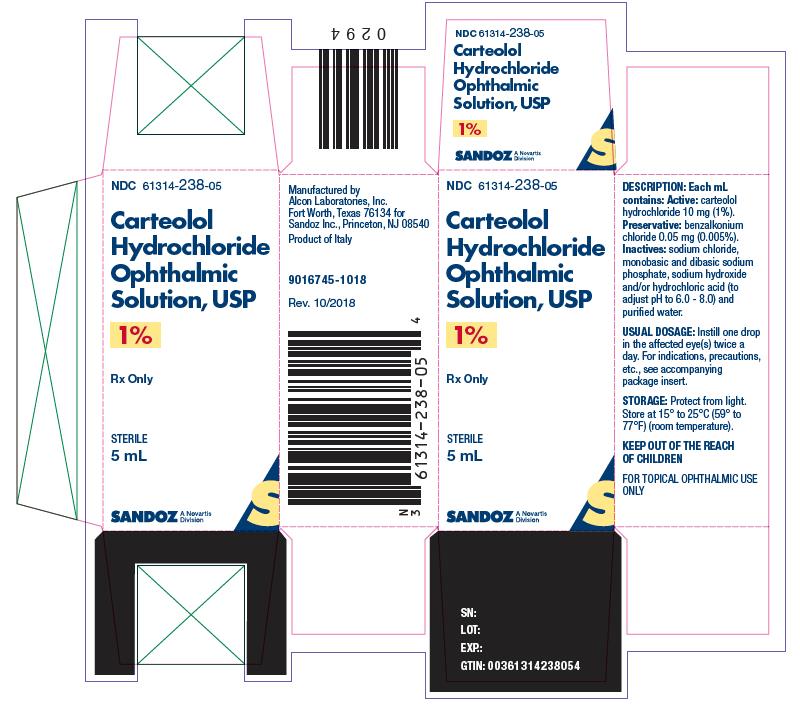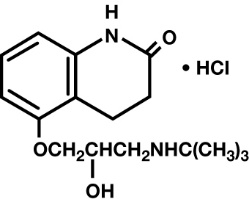 DRUG LABEL: Carteolol Hydrochloride
NDC: 61314-238 | Form: SOLUTION
Manufacturer: Sandoz Inc
Category: prescription | Type: HUMAN PRESCRIPTION DRUG LABEL
Date: 20210831

ACTIVE INGREDIENTS: CARTEOLOL HYDROCHLORIDE 10 mg/1 mL
INACTIVE INGREDIENTS: BENZALKONIUM CHLORIDE; SODIUM CHLORIDE; SODIUM PHOSPHATE, MONOBASIC, UNSPECIFIED FORM; SODIUM PHOSPHATE, DIBASIC, UNSPECIFIED FORM; SODIUM HYDROXIDE; HYDROCHLORIC ACID; WATER

Carteolol Hydrochloride Ophthalmic Solution USP, 1%
Rx Only
Sterile

DESCRIPTION

Carteolol Hydrochloride Ophthalmic Solution USP, 1% is a nonselective beta-adrenoceptor blocking agent for ophthalmic use.

The chemical name for carteolol hydrochloride is (±)-5-[3-[(1,1-dimethylethyl) amino]-2-hydroxypropoxy]-3,4-dihydro-2(1H)-quinolinone monohydrochloride. The structural formula is as follows:

C16H24N2O3•HCI Mol. Wt. 328.84

Each mL of sterile solution contains Active: carteolol hydrochloride 10 mg (1%). Preservative: benzalkonium chloride 0.05 mg (0.005%). Inactives: sodium chloride, monobasic and dibasic sodium phosphate, sodium hydroxide and/or hydrochloric acid (to adjust pH to 6.0 - 8.0) and purified water.

CLINICAL PHARMACOLOGY

Carteolol is a nonselective beta-adrenergic blocking agent with associated intrinsic sympathomimetic activity and without significant membrane-stabilizing activity.

Carteolol Hydrochloride reduces normal and elevated intraocular pressure (IOP) whether or not accompanied by glaucoma. The exact mechanism of the ocular hypotensive effect of beta-blockers has not been definitely demonstrated.

In general, beta-adrenergic blockers reduce cardiac output in patients in good and poor cardiovascular health. In patients with severe impairment of myocardial function, beta-blockers may inhibit the sympathetic stimulation necessary to maintain adequate cardiac function. Beta-adrenergic blockers may also increase airway resistance in the bronchi and bronchioles due to unopposed parasympathetic activity.

Given topically twice daily in controlled domestic clinical trials ranging from 1.5 to 3 months, Carteolol Hydrochloride produced a median percent reduction of IOP 22% to 25%. No significant effects were noted on corneal sensitivity, tear secretion, or pupil size.

INDICATIONS AND USAGE

Carteolol Hydrochloride Ophthalmic Solution 1% has been shown to be effective in lowering intraocular pressure and may be used in patients with chronic open-angle glaucoma and intraocular hypertension. It may be used alone or in combination with other intraocular pressure lowering medications.

CONTRAINDICATIONS

Carteolol is contraindicated in those individuals with bronchial asthma or with a history of bronchial asthma, or severe chronic obstructive pulmonary disease (see WARNINGS); sinus bradycardia; second- and third-degree atrioventricular block; overt cardiac failure (see WARNINGS); cardiogenic shock; or hypersensivity to any component of this product.

WARNINGS

Carteolol has not been detected in plasma following ocular instillation. However, as with other topically applied ophthalmic preparations, Carteolol may be absorbed systemically. The same adverse reactions found with systemic administration of beta-adrenergic blocking agents may occur with topical administration. For example, severe respiratory reactions and cardiac reactions, including death due to bronchospasm in patients with asthma, and rarely death in association with cardiac failure, have been reported with topical application of beta-adrenergic blocking agents (see CONTRAINDICATIONS).

Cardiac Failure: Sympathetic stimulation may be essential for support of the circulation in individuals with diminished myocardial contractility, and its inhibition by beta-adrenergic receptor blockade may precipitate more severe failure.

In Patients Without a History of Cardiac Failure: Continued depression of the myocardium with beta-blocking agents over a period of time can, in some cases, lead to cardiac failure. At the first sign or symptom of cardiac failure, Carteolol Hydrochloride should be discontinued.

Non-Allergic Bronchospasm: In patients with non-allergic bronchospasm or with a history of non-allergic bronchospasm (e.g., chronic bronchitis, emphysema), Carteolol Hydrochloride Ophthalmic Solution should be administered with caution since it may block bronchodilation produced by endogenous and exogenous catecholamine stimulation of beta2 receptors.

Major Surgery: The necessity or desirability of withdrawal of beta-adrenergic blocking agents prior to major surgery is controversial. Beta-adrenergic receptor blockade impairs the ability of the heart to respond to beta-adrenergically mediated reflex stimuli. This may augment the risk of general anesthesia in surgical procedures. Some patients receiving beta-adrenergic receptor blocking agents have been subject to protracted severe hypotension during anesthesia. For these reasons, in patients undergoing elective surgery, gradual withdrawal of beta-adrenergic receptor blocking agents may be appropriate.

If necessary during surgery, the effects of beta-adrenergic blocking agents may be reversed by sufficient doses of such agonists as isoproterenol, dopamine, dobutamine or levarterenol (see OVERDOSAGE).

Diabetes Mellitus: Beta-adrenergic blocking agents should be administered with caution in patients subject to spontaneous hypoglycemia or to diabetic patients (especially those with labile diabetes) who are receiving insulin or oral hypoglycemic agents. Beta-adrenergic receptor blocking agents may mask the signs and symptoms of acute hypoglycemia.

Thyrotoxicosis: Beta-adrenergic blocking agents may mask certain clinical signs (e.g., tachycardia) of hyperthyroidism. Patients suspected of developing thyrotoxicosis should be managed carefully to avoid abrupt withdrawal of beta-adrenergic blocking agents which might precipitate a thyroid storm.

PRECAUTIONS

General

Carteolol Hydrochloride Ophthalmic Solution should be used with caution in patients with known hypersensitivity to other beta-adrenoceptor blocking agents.

Use with caution in patients with known diminished pulmonary function.

In patients with angle-closure glaucoma, the immediate objective of treatment is to reopen the angle. This requires constricting the pupil with a miotic. Carteolol has little or no effect on the pupil. When Carteolol is used to reduce elevated intraocular pressure in angle-closure glaucoma, it should be used with a miotic and not alone.

Information to the Patient

For topical use only. To prevent contaminating the dropper tip and solution, care should be taken not to touch the eyelids or surrounding areas with the dropper tip of the bottle. Keep bottle tightly closed when not in use. Protect from light.

Risk from Anaphylactic Reaction

While taking beta-blockers, patients with a history of atopy or a history of severe anaphylactic reaction to a variety of allergens may be more reactive to repeated accidental, diagnostic or therapeutic challenge with such allergens. Such patients may be unresponsive to the usual doses of epinephrine used to treat anaphylactic reactions.

Muscle Weakness

Beta-adrenergic blockade has been reported to potentiate muscle weakness consistent with certain myasthenic symptoms (e.g., diplopia, ptosis and generalized weakness).

Drug Interactions

Carteolol Hydrochloride Ophthalmic Solution should be used with caution in patients who are receiving a beta-adrenergic blocking agent orally, because of the potential for additive effects on systemic beta-blockade.

Close observation of the patient is recommended when a beta-blocker is administered to patients receiving catecholamine-depleting drugs such as reserpine, because of possible additive effects and the production of hypotension and/or marked bradycardia, which may produce vertigo, syncope, or postural hypotension.

Carcinogenesis, Mutagenesis, Impairment of Fertility

Carteolol hydrochloride did not produce carcinogenic effects at doses up to 40 mg/kg/day in two-year oral rat and mouse studies. Test of mutagenicity, including the Ames Test, recombinant (rec)-assay, in vivo cytogenetics and dominant lethal assay demonstrated no evidence for mutagenic potential. Fertility of male and female rats and male and female mice was unaffected by administration of carteolol hydrochloride dosages up to 150 mg/kg/day.

Teratogenic Effects

Pregnancy Category C: Carteolol hydrochloride increased resorptions and decreased fetal weights in rabbits and rats at maternally toxic doses approximately 1052 and 5264 times the maximum recommended human oral dose (10 mg/70 kg/day), respectively. A dose-related increase in wavy ribs was noted in the developing rat fetus when pregnant females received daily doses of approximately 212 times the maximum recommended human oral dose. No such effects were noted in pregnant mice subjected to up to 1052 times the maximum recommended human oral dose. There are no adequate and well-controlled studies in pregnant women. Carteolol Hydrochloride Ophthalmic Solution should be used during pregnancy only if the potential benefit justifies the potential risk to the fetus.

Nursing Mothers

It is not known whether this drug is excreted in human milk, although in animal studies carteolol has been shown to be excreted in breast milk. Caution should be exercised when Carteolol Hydrochloride Ophthalmic Solution is administered to nursing mothers.

Pediatric Use

Safety and effectiveness in pediatric patients have not been established.

ADVERSE REACTIONS

The following adverse reactions have been reported in clinical trials with Carteolol Hydrochloride Ophthalmic Solution.

Ocular: Transient eye irritation, burning, tearing, conjunctival hyperemia and edema occurred in about 1 of 4 patients. Ocular symptoms including blurred and cloudy vision, photophobia, decreased night vision, and ptosis and ocular signs including blepharoconjunctivitis, abnormal corneal staining, and corneal sensitivity occurred occasionally.

Systemic: As is characteristic of nonselective adrenergic blocking agents, Carteolol may cause bradycardia and decreased blood pressure (See WARNINGS). The following systemic events have occasionally been reported with the use of Carteolol Hydrochloride Ophthalmic Solution: cardiac arrhythmia, heart palpitation, dyspnea, asthenia, headache, dizziness, insomnia, sinusitis, and taste perversion.

The following additional adverse reactions have been reported with ophthalmic use of beta1 and beta2 (nonselective) adrenergic receptor blocking agents:

Body As a Whole: Headache

Cardiovascular: Arrhythmia, syncope, heart block, cerebral vascular accident, cerebral ischemia, congestive heart failure, palpitation (see WARNINGS).

Digestive: Nausea

Psychiatric: Depression

Skin: Hypersensitivity, including localized and generalized rash

Respiratory: Bronchospasm (predominantly in patients with pre-existing bronchospastic disease), respiratory failure (see WARNINGS)

Endocrine: Masked symptoms of hypoglycemia in insulin-dependent diabetics (see WARNINGS)

Special Senses: Signs and symptoms of keratitis, blepharoptosis, visual disturbances including refractive changes (due to withdrawal of miotic therapy in some cases), diplopia, ptosis.

Other reactions associated with the oral use of nonselective adrenergic receptor blocking agents should be considered potential effects with ophthalmic use of these agents.

OVERDOSAGE

No specific information on emergency treatment of overdosage in humans is available. Should accidental ocular overdosage occur, flush eye(s) with water or normal saline. The most common effects expected with overdosage of a beta-adrenergic blocking agent are bradycardia, bronchospasm, congestive heart failure and hypotension.

In case of ingestion, treatment with Carteolol Hydrochloride Ophthalmic Solution should be discontinued and gastric lavage considered. The patient should be closely observed and vital signs carefully monitored. The prolonged effects of carteolol must be considered when determining the duration of corrective therapy. On the basis of the pharmacologic profile, the following additional measures should be considered as appropriate:

Symptomatic Sinus Bradycardia or Heart Block: Administer atropine. If there is no response to vagal blockade, administer isoproterenol cautiously.

Bronchospasm: Administer a beta2-stimulating agent such as isoproterenol and/or a theophylline derivative.

Congestive Heart Failure: Administer diuretics and digitalis glycosides as necessary.

Hypotension: Administer vasopressors such as intravenous dopamine, epinephrine or norepinephrine bitartrate.

DOSAGE AND ADMINISTRATION

The usual dose is one drop of Carteolol Hydrochloride Ophthalmic Solution 1% in the affected eye(s) twice a day.

If the patient's IOP is not at a satisfactory level on this regimen, concomitant therapy with pilocarpine and other miotics, and/or epinephrine or dipivefrin, and/or systemically administered carbonic anhydrase inhibitors, such as acetazolamide, can be instituted.

HOW SUPPLIED

Carteolol Hydrochloride Ophthalmic Solution USP, 1% is supplied as a sterile ophthalmic solution in plastic dispenser bottles of 5 mL (NDC 61314-238-05), 10 mL (NDC 61314-238-10) and 15 mL (NDC 61314-238-15).

Store at 15° to 25°C (59° to 77°F) (room temperature) and protect from light.

Manufactured by
Alcon Laboratories, Inc.
Fort Worth, Texas 76134 for
Sandoz Inc.
Princeton, NJ 08540

300049856-0821

Rev. August 2021

Printed in USA

PRINCIPAL DISPLAY PANEL

NDC 61314-238-05

Carteolol

Hydrochloride

Ophthalmic

Solution, USP

1%

Rx only
STERILE
5 mL

SANDOZ